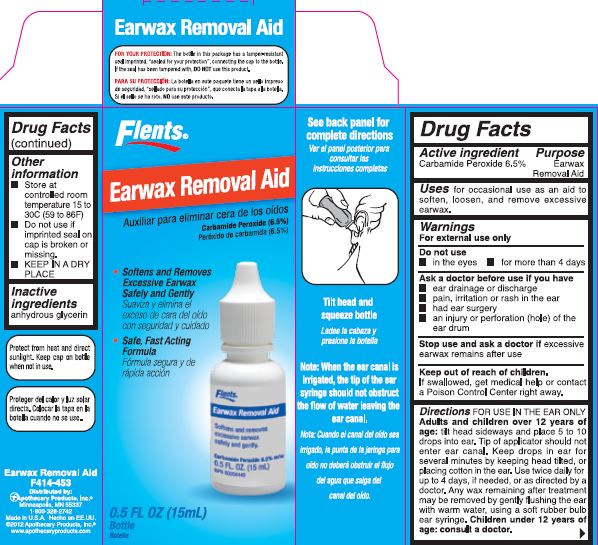 DRUG LABEL: Earwax Removal Aid
NDC: 49762-453 | Form: LIQUID
Manufacturer: Apothecary Products, LLC
Category: otc | Type: HUMAN OTC DRUG LABEL
Date: 20140524

ACTIVE INGREDIENTS: CARBAMIDE PEROXIDE 6.5 mg/100 mL
INACTIVE INGREDIENTS: GLYCERIN 120.0 mg/100 mL

Earwax Removal Aid

Active ingredient(s)

Carbamide Peroxide 6.5%

Purpose

Earwax Removal Aid

Use(s)

For occasional use to soften, loosen and remove excessive earwax.

Warnings

Warning

For External Use Only

Do not use

- In the eye
- for more than 4 days

Ask a doctor before use if you have

- ear drainage or discharge
- pain, irritation or rash in the ear
- had ear surgery
- an injury or perforation (hole) in the ear drum

Stop use and ask a doctor if excessive earwax remains after use

Keep out of reach of children

If swallowed, get medical help or contact a Poison Control Center right away.

Directions

FOR USE IN THE EAR ONLY

Adults and children 12 years of age: tilt head sideways and place 5 to 10 drops into ear. Tip of applicator should not enter ear canal. Keep drops in ear for several minutes by keeping head tilted, or placing cotton in the ear. Use twice daily for up to 4 days, if needed, or as directed by a doctor. Any wax remaining after treatment my be removed by gently flushing the ear with warm water, using a soft rubber bulb ear syringe. Children under 12 years of age, consult a doctor.

Other information

Do not use if imprinted seal on cap is broken or missing.

Storage

- Store at controlled room temperature 15 to 30C (59 to 86F)
- KEEP IN A DRY PLACE

Principal Display Panel

Principle display panel:

Flents Earwax Removal Aid Box

Inactive Ingredients

anhydrous Glycerin